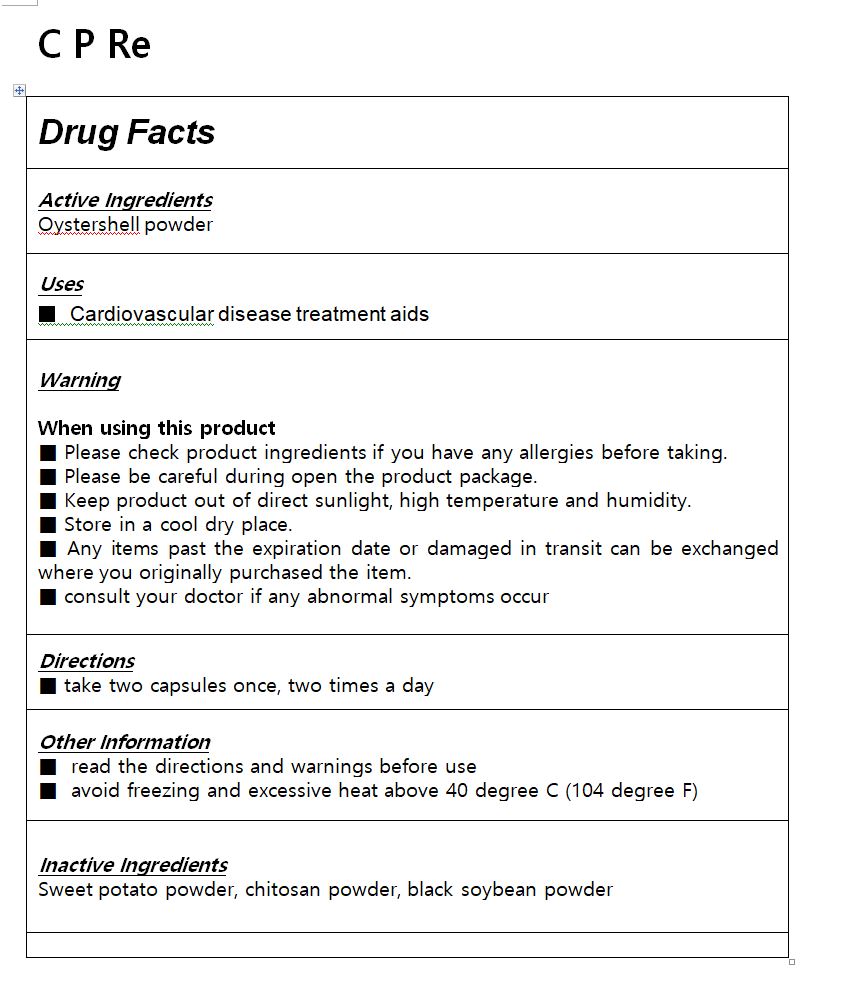 DRUG LABEL: C P Re
NDC: 81445-0007 | Form: TABLET
Manufacturer: coexleaders co.,ltd.
Category: otc | Type: HUMAN OTC DRUG LABEL
Date: 20210304

ACTIVE INGREDIENTS: CALCIUM 0.8 1/1 1
INACTIVE INGREDIENTS: SOYBEAN

ACTIVE INGREDIENT

Oystershell powder

INACTIVE INGREDIENT

Sweet potato powder, chitosan powder, black soybean powder

PURPOSE

Cardiovascular disease treatment aids

KEEP OUT OF REACH OF CHILDREN

WARNING

Please check product ingredients if you have any allergies before taking.

Please be careful during open the product package.

Keep product out of direct sunlight, high temperature and humidity.

Store in a cool dry place.

Any items past the expiration date or damaged in transit can be exchanged where you originally purchased the item.

consult your doctor if any abnormal symptoms occur

USES

for oral use only

INDICATION & USAGE SECTION

take two capsules once, two times a day